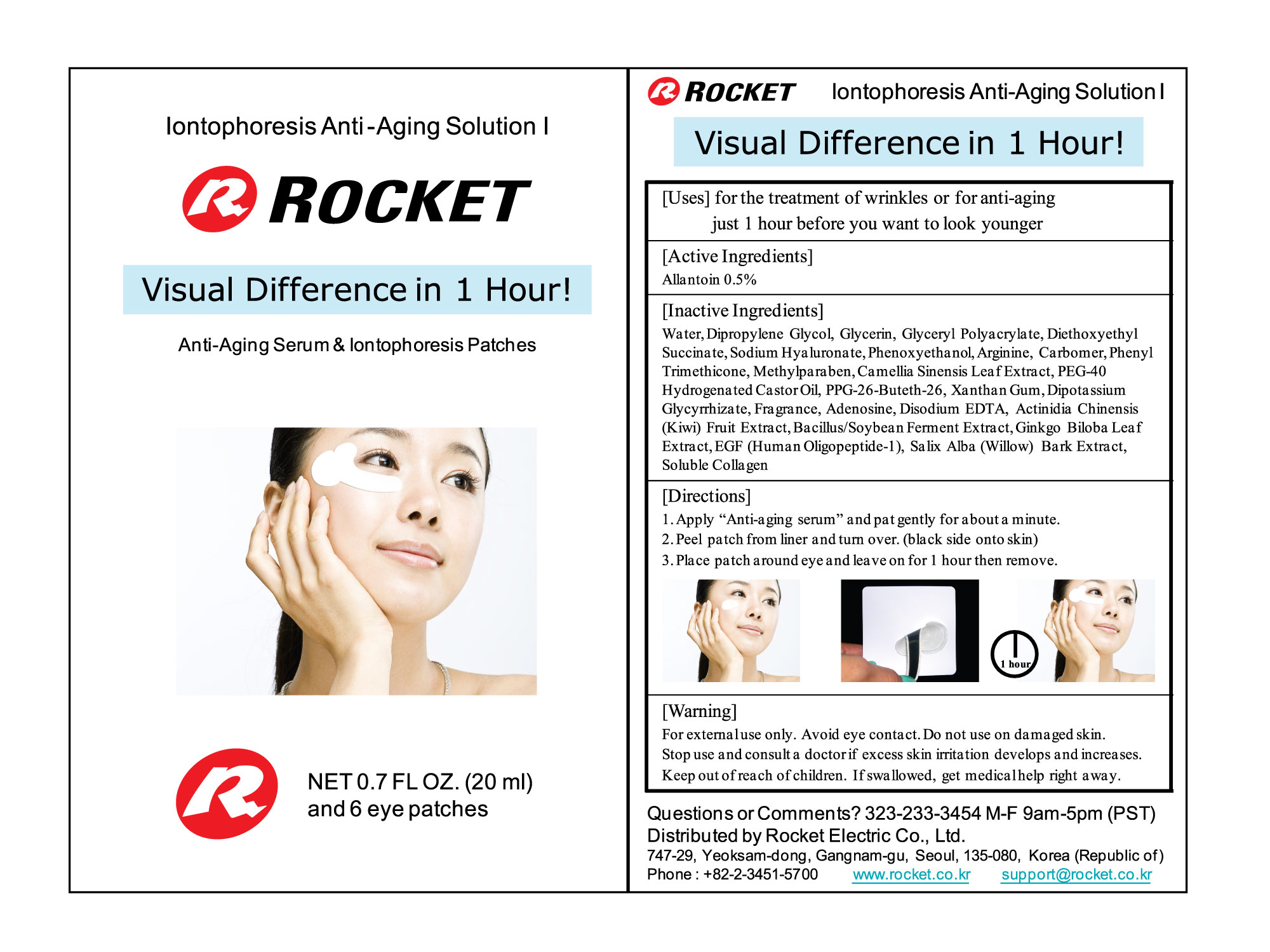 DRUG LABEL: IONTOPHORESIS
NDC: 51985-010 | Form: LOTION
Manufacturer: ROCKET ELECTRIC CO., LTD.
Category: otc | Type: HUMAN OTC DRUG LABEL
Date: 20110207

ACTIVE INGREDIENTS: ALLANTOIN 0.1 mL/20 mL
INACTIVE INGREDIENTS: WATER; DIPROPYLENE GLYCOL; GLYCERIN; HYALURONATE SODIUM; PHENOXYETHANOL; ARGININE; PHENYL TRIMETHICONE; METHYLPARABEN; XANTHAN GUM; ADENOSINE; EDETATE DISODIUM

Drug Facts

Active Ingredient: Allantoin

Inactive Ingredients:
WATER, DIPROPYLENE GLYCOL, GLYCERIN, GLYCERYL POLYACRYLATE, DIETHOXYETHYL SUCCINATE, SODIUM HYALURONATE, PHENOXYETHANOL, ARGININE, CARBOMER,
PHENYL TRIMETHICONE, METHYLPARABEN, CAMELLIA SINENSIS LEAF EXTRACT, PEG-40 HYDROGENATED CASTOR OIL, PPG-26-BUTETH-26, XANTHAN GUM, DIPOTASSIUM GLYCYRRHIZATE, FRAGRANCE, ADENOSINE, DISODIUM EDTA, ACTINIDIA CHINENSIS (KIWI) FRUIT EXTRACT, BACILLUS/SOYBEAN FERMENT EXTRACT, GINKO BILOBA LEAF EXTRACT, HUMAN OLIGOPEPTIDE-1, SALIX ALBA (WILLOW) BARK EXTRACT, SOLUBLE COLLAGEN

Purpose:
For the treatment of wrinkles or for anti aging just 1 hour before you want to look younger.

WARNINGS

Wanrings:
For external use only.
Avoid eye contact.
Do not use on damage skin.
Stop use consult a doctor if excess skin irritation develops and increases.

Keep out of reach of children:
If swallowed, get medical help right away.

Directions:
Apply Anti aging serum and pat gently for about a minute.
Peel patch from liner and turn over. black side onto skin.
Place patch around eye and leave on for 1 hour then remove.

Dosage and administration:
Apply Anti aging serum and pat gently for about a minute.
Peel patch from liner and turn over. black side onto skin.
Place patch around eye and leave on for 1 hour then remove.